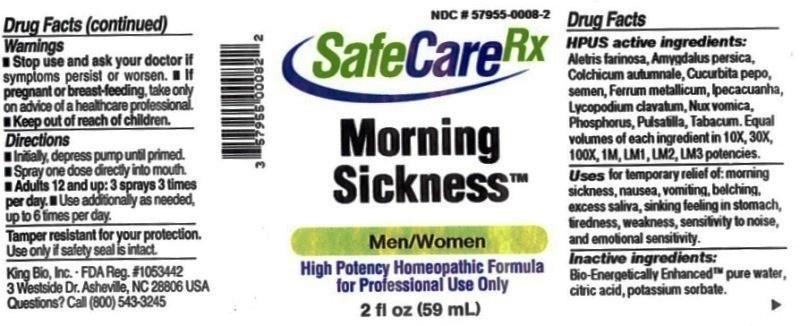 DRUG LABEL: Morning Sickness
NDC: 57955-0008 | Form: LIQUID
Manufacturer: King Bio Inc.
Category: homeopathic | Type: HUMAN OTC DRUG LABEL
Date: 20150309

ACTIVE INGREDIENTS: ALETRIS FARINOSA ROOT 10 [hp_X]/59 mL; PRUNUS PERSICA FLOWER 10 [hp_X]/59 mL; COLCHICUM AUTUMNALE BULB 10 [hp_X]/59 mL; PUMPKIN SEED 10 [hp_X]/59 mL; IRON 10 [hp_X]/59 mL; IPECAC 10 [hp_X]/59 mL; LYCOPODIUM CLAVATUM SPORE 10 [hp_X]/59 mL; STRYCHNOS NUX-VOMICA SEED 10 [hp_X]/59 mL; PHOSPHORUS 10 [hp_X]/59 mL; PULSATILLA VULGARIS 10 [hp_X]/59 mL; TOBACCO LEAF 10 [hp_X]/59 mL
INACTIVE INGREDIENTS: WATER; ANHYDROUS CITRIC ACID; POTASSIUM SORBATE

Morning Sickness™

ACTIVE INGREDIENT

Drug Facts__________________________________________________________________________________________________________

HPUS active ingredients: Aletris farinosa, Amygdalus persica, Colchicum autumnale, Cucurbita pepo, semen, Ferrum metallicum, Ipecacuanha, Lycopodium clavatum, Nux vomica, Phosphorus, Pulsatilla, Tabacum. Equal volumes of each ingredient in 10X, 30X, 100X, 1M, LM1, LM2, LM3 potencies.

INDICATIONS AND USAGE

Uses for temporary relief of: morning sickness, nausea, vomiting, belching, excess saliva, sinking feeling in stomach, tiredness, weakness, sensitivity to noise, and emotional sensitivity.

Inactive Ingredients:

Bio-Energetically Enhanced™ pure water, citric acid and potassium sorbate.

Warnings

- Stop use and ask your doctor if symptoms persist or worsen.
- If pregnant or breast-feeding, take only on advice of a healthcare professional.

- Keep out of reach of children.

Directions

- Initially, depress pump until primed.
- Spray one dose directly into mouth.
- Adults 12 and up: 3 sprays 3 times per day
- Use additionally as needed, up to 6 times per day.

OTHER SAFETY INFORMATION

Tamper resistant for your protection. Use only if safety seal is intact.

PURPOSE

Uses for temporary relief of:

- morning sickness
- nausea
- vomiting
- belching
- excess saliva
- sinking feeling in stomach
- tiredness
- weakness
- sensitivity to noise
- emotional sensitivity